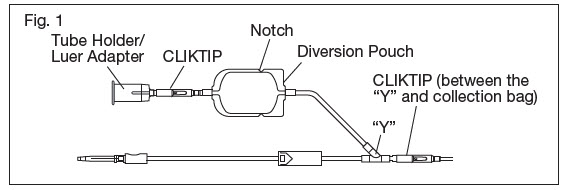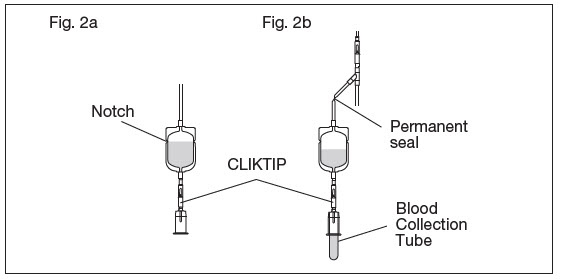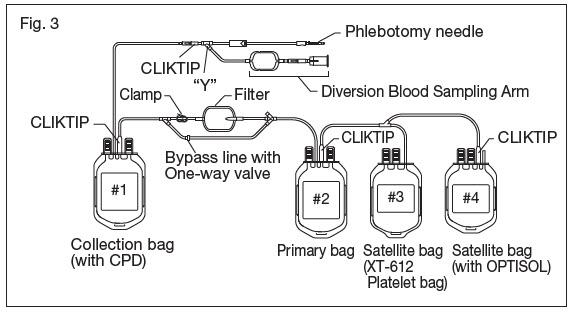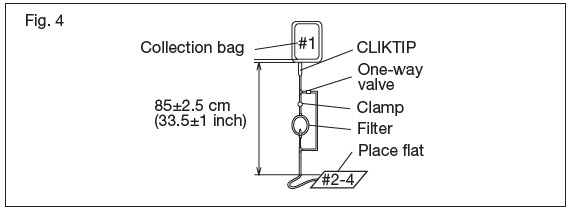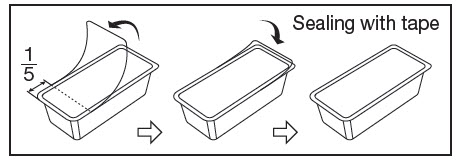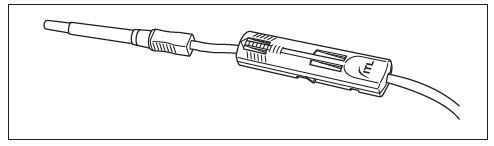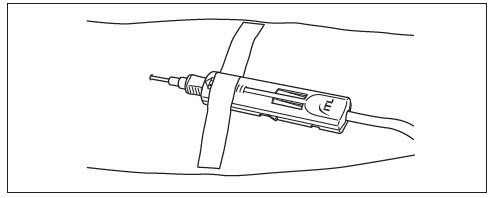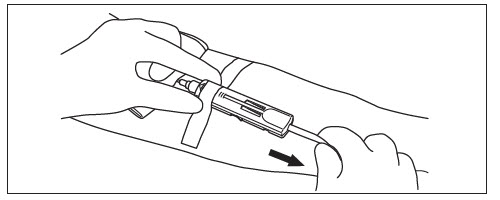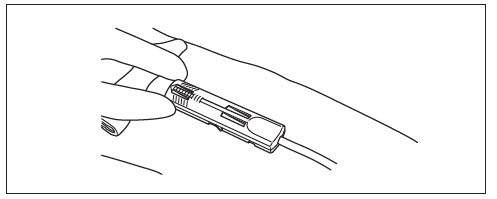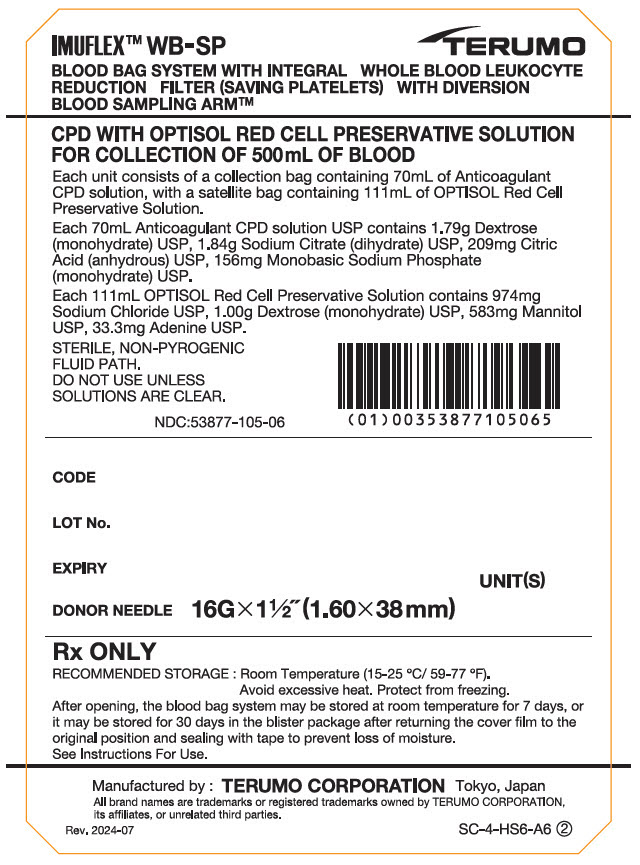 DRUG LABEL: IMUFLEX WB-SP Blood Bag System with Integral Whole Blood Leukocyte Reduction Filter (Saving Platelets) with Diversion Blood Sampling Arm Anticoagulant Citrate Phosphate Dextrose (CPD) and OPTISOL (AS-5) Red Cell Preservative for collection of 500mL of Blood
NDC: 53877-105 | Form: KIT | Route: INTRAVENOUS
Manufacturer: Terumo Corporation
Category: prescription | Type: HUMAN PRESCRIPTION DRUG LABEL
Date: 20241217

ACTIVE INGREDIENTS: DEXTROSE MONOHYDRATE 25.5 g/1000 mL; TRISODIUM CITRATE DIHYDRATE 26.3 g/1000 mL; SODIUM PHOSPHATE, MONOBASIC, UNSPECIFIED FORM 2.22 g/1000 mL; ANHYDROUS CITRIC ACID 2.99 g/1000 mL; Dextrose Monohydrate 900 mg/100 mL; Sodium Chloride 877 mg/100 mL; Mannitol 525 mg/100 mL; Adenine 30 mg/100 mL
INACTIVE INGREDIENTS: Water; Water

IMUFLEX™ WB-SP BLOOD BAG SYSTEM with Integral Whole Blood Leukocyte Reduction Filter (Saving Platelets) with Diversion Blood Sampling Arm™

Rev. 2020-09
N-SP-OP-A-DB ③

CPD/OPTISOL™ SOLUTION

For the collection of 500 mL of Whole Blood

FULL PRESCRIBING INFORMATION

*Sections or subsections omitted from the Full Prescribing Information are not listed [includes sections 4, 6, 7, 8, 9, 10, 12, 13, 14, 15 and 17].

1. INDICATIONS AND USAGE

1.1. Read these instructions carefully before use.

1.2. Rx ONLY.

1.3. Intended for the collection, processing and preservation of Whole Blood and blood components. Not intended for direct intravenous infusion.

1.4. For the collection of 500 mL ±10% Whole Blood.

1.5. Integral Diversion Blood Sampling Arm is intended to divert and obtain donor samples for laboratory testing prior to collection of the Whole Blood unit.

1.6. Integral filter unit intended for leukocyte reduction of Whole Blood up to 8 hours after blood collection when Whole Blood is stored at ambient temperature.

1.7. For further processing, use standard component processing techniques.

2. DOSAGE AND ADMINISTRATION

2.1. To open blister package, peel cover film back 4/5 of its length.

2.2. Prepare the blood bag following your institution's standard operating procedures.

2.2.1. Materials Needed : Evacuated blood collection tubes (glass or plastic)

2.3. Make a loose knot in the donor tubing below the "Y" and CLIKTIP (inline closure device) unless alternate methods are used to seal the tubing at the end of collection.

2.4. Temporarily clamp donor tubing between the phlebotomy needle and the "Y".

2.5. Suspend the collection bag as far as possible below the donor's arm.

2.6. Apply blood pressure cuff or tourniquet to donor's arm. Disinfect site of phlebotomy. If blood pressure cuff is used, inflate to approximately 60 mmHg.

2.7. Remove the needle cover and perform phlebotomy. Remove the temporary clamp on the donor tubing to permit blood flow into the Diversion Blood Sampling Arm pouch.

2.7.1. CAUTION: Do not touch the needle after removing the needle cover.

2.8. Secure the needle safety device in place following the device instructions provided on the reverse side.

2.9. Secure donor tubing to donor's arm.

2.10. Position the diversion pouch with the notches up and the Tube Holder/Luer Adapter assembly down. When the level of blood in the pouch is approximately in line with the notches, the diversion pouch is full. (Fig. 2a)

2.10.1. NOTE: The approximate fill volume of the pouch at the notches is 35 mL.

2.11. Permanently seal the tubing between the "Y" and the diversion pouch to maintain a closed system using an aluminum clip or a tube sealer approved for use with tubing connected to a donor (Fig. 2b).

2.11.1. CAUTION: Do not use a dielectric tube sealer to seal the tubing while the needle is connected to the donor's body unless it is approved for such a purpose.

2.12. To initiate blood flow into the collection bag, break the CLIKTIP between the "Y" and the collection bag.

2.13. To avoid clot formation, collect samples as soon as possible from the diversion pouch as follows (Fig. 2b).

2.13.1. CAUTION: Do not collect donor test samples until the tubing between the "Y" and the diversion pouch is permanently sealed.

2.13.2. Break the CLIKTIP in the tubing below the pouch to open the pathway for sampling. (Fig. 2b)

2.13.3. Position the diversion pouch with the notches up and the Tube Holder/Luer Adapter assembly downward. Assure that any air in the pouch is at the top and will not enter the blood collection tubes.

2.13.4. Open the Tube Holder lid and insert blood collection tube firmly into the tube holder; when full, remove sample tube from holder. Repeat to collect additional samples.

2.13.5. NOTE: The pouch may be removed after the donor test samples are collected. A second seal must be made between the diversion pouch and the permanent seal prior to removing the pouch.

2.14. Mix blood with anticoagulant in the collection bag and continue to mix at several intervals during collection and immediately after collection. If using an automated mixer, follow manufacturer's instructions.

2.15. Collect labeled volume of blood 500 mL ±10%.

2.16. When the desired amount of blood has been collected, seal the tubing or tighten the loose knot (white knot) prepared in Step 2.3. Make a second seal between the first seal or knot and the "Y". Various methods may be used to seal tubing.

2.17. Release pressure on the donor's arm and remove the needle into the needle safety device following the device instructions provided on the reverse side. Sever the donor tubing between the two seals previously made below the CLIKTIP and "Y".

2.17.1. CAUTION: Discard the Diversion Blood Sampling Arm and phlebotomy needle/donor tubing according to institutional standard operating procedures.

2.18. Seal and remove donor tubing from collection bag or strip donor tubing as follows:

2.18.1. To obtain a quality control prefiltration sample, strip blood from donor tubing into collection bag, mix well, and allow tubing to refill; repeat once. To prevent the blood from clotting in the tubing, work quickly as possible. Leave an adequate length of tubing containing the well-mixed anticoagulated whole blood attached to the collection bag.

2.18.2. Or, to maximize collection recovery, strip the tubing, mix well and seal tubing close to the collection bag without refilling. To prevent the blood from clotting in the tubing, work quickly as possible. Remove tubing from collection bag.

2.19. The blood filtration is executed according to the following operation. (see Fig.3 and Fig.4)

2.19.1. NOTE: Wait 1 hour after collection before filtering. Filtration can be accomplished when blood is stored at room temperature for up to eight hours after collection.

2.19.2. NOTE: The band guides used to bundle the coiled tubing to prevent entanglement during shipping should be removed prior to filtration (not depicted).

2.20. Mix the unfiltered whole blood unit by inverting the collection bag #1 (pre-filter bag) several times.

2.21. Hang the collection bag #1, and extend the filtration set to 85 ± 2.5 cm or 33.5 ± 1 inch. Verify that the filter is vertical and ensure all tubing is freely suspended. Position and support bags #2-4 on a flat surface (Fig. 4).

2.21.1. NOTE: This distance is measured from the outlet of the collection bag to the position of the supported bags as indicated in Fig. 4.

2.21.2. NOTE: Verity tubing has been removed from the tube guides and extends freely.

2.22. Break the CLIKTIP at the outlet of the collection bag #1, and start filtration.

2.22.1. CAUTION: Do not squeeze the collection bag during filtration.

2.22.2. CAUTION: Do not squeeze or apply pressure on the filter while it is attached to the bag containing the filtered blood.

2.22.3. CAUTION: If for any reason whole blood passes through the one-way valve, stop filtration immediately and consider the product as non-leukocyte reduced.

2.23. Filtration ends when the collection bag is empty or blood flow has stopped. Close the WHITE clamp above the filter.

2.24. Expel air through the bypass line and back into the empty collection bag #1 by holding the primary bag #2 upright so that the air will be closest to the ports. Gently squeeze the primary bag containing the leukoreduced whole blood until filtered blood reaches the "Y" below the filter. To ensure ease of air removal ensure primary bag #2 is below the filter outlet.

2.25. Open the WHITE clamp.

2.26. Recovery of filtered Whole Blood is complete when the collection bag and the inlet side of the filter have drained or blood flow has stopped. Close the WHITE clamp.

2.27. Seal the tubing as close as possible to the "Y" below the filter and properly dispose of the filter and collection bag #1.

2.28. Strip the post filter tubing into the primary bag #2, mix well, and allow tubing to refill; repeat once. Make an appropriate number of segments of anticoagulated blood for testing by sealing on or near the X marks. Leave segments attached to the filtered whole blood unit.

2.29. The time between Whole Blood collection and component separation may vary depending on both the blood bag system and processing options selected.

2.29.1. NOTE: Platelets should be separated from the Red Blood Cells within 8 hours of blood collection.

2.29.2. NOTE: Fresh Frozen Plasma should be separated from the Red Blood Cells and placed in a freezer at –18ºC or colder within 8 hours of collection.

2.29.3. NOTE: OPTISOL should be added to the Red Blood Cells immediately after removal of the plasma. If plasma is not separated from the Red Blood Cells within 8 hours, OPTISOL may be added within 72 hours of collection if Whole Blood is refrigerated.

2.29.4. NOTE: Other plasma components may be prepared following approved regulations and standards.

2.30. Follow your institution's standard component processing procedures to prepare components.

2.31. Centrifuge filtered whole blood unit to separate red blood cells from platelet rich plasma.

2.32. Break the CLIKTIP of primary bag #2 and transfer leukocytes-reduced platelet rich plasma into XT-612 Platelet bag #3. Clamp the transfer tubing on the Platelet bag.

2.33. Break the CLIKTIP of the OPTISOL bag #4 and drain contents into primary bag #2 containing red blood cells. Seal tubing of primary bag in two places, and cut between seals and separate from Platelet and OPTISOL bags.

2.33.1. NOTE: Empty OPTISOL bag is used for further component preparation.

2.34. Invert the red blood cell – OPTISOL mixture several times to assure the final product is well suspended.

2.35. Store AS-5 Red Blood Cells, Leukocytes Reduced between 1-6°C for up to 42 days.

2.35.1. NOTE: Whole Blood or Red Blood Cells in CPD may be stored for up to 21 days at 1-6°C.

2.36. Store Platelets, Leukocytes Reduced between 20-24°C, maintaining a continuous gentle agitation, for up to 5 days in XT-612 bag.

3. DOSAGE FORMS AND STRENGTHS

3.1. 70 mL Citrate Phosphate Dextrose (CPD) anticoagulant USP for collection of 500 mL Whole Blood. Each 70 mL contains 1.79 g Dextrose (monohydrate) USP, 1.84 g Sodium Citrate (dihydrate) USP, 209 mg Citric Acid (anhydrous) USP, 156 mg Monobasic Sodium Phosphate (monohydrate) USP.

3.2. 111 mL OPTISOL Red Cell Preservative Solution. Each 111 mL contains 974 mg Sodium Chloride USP, 1.00g Dextrose (monohydrate) USP, 583 mg Mannitol USP, 33.3 mg Adenine USP.

5. WARNINGS AND PRECAUTIONS

5.1. Rx ONLY.

5.2. Do not use unless solutions are clear and free from particulates.

5.3. Always inspect the blood bag set for leaks before use.

5.4. Avoid excessive heat and direct sunlight. Protect from freezing.

5.5. Recommended storage conditions: Room Temperature (15-25°C/59-77°F).

5.6. It is normal to have condensation in the blister packaging. If the amount of moisture is greater than expected, check for leaks from the fluid-filled components of the blood bag set.

5.7. Use aseptic techniques.

5.8. Do not use a dielectric tube sealer to seal the tubing while the needle is connected to the donor's body unless it is approved for such a purpose.

5.9. Do not touch needle after removing the needle cover.

5.10. Do not collect donor test samples until the tubing between the "Y" and the diversion pouch is permanently sealed.

5.11. Discard the Diversion Blood Sampling Arm and phlebotomy needle/donor tubing according to institutional standard operating procedures.

5.12. The AGELESS oxygen absorber packet, (Mitsubishi Gas Chemical) contained in this package absorbs oxygen and generates heat on removal. Do not open and handle it with care.

5.13. Dispose of the AGELESS packet with the blister tray.

5.14. Do not dispose the AGELESS packet with wastes containing volatile or flammable materials.

5.15. Due to possible exposure to infectious agents in the handling of blood, take adequate precautions at all times to prevent exposure to and transmission of such agents. Follow your institution's standard operating procedures.

11. DESCRIPTION / PRODUCT SPECIFICATIONS

11.1. This blood bag system includes a 16 gauge x 1 1/2 inch (1.60 × 38 mm) needle with needle cover and a 500mL (nominal capacity 600mL) collection bag containing 70mL Citrate Phosphate Dextrose (CPD) anticoagulant. The Quadruple blood bag set has one integrally attached empty primary bag, one empty XT-612 5 day Platelet bag, and one satellite bag containing 111 mL OPTISOL Red Cell Preservative Solution.

11.2. Blood bag codes ending in A6 are the collection set with an Integral Diversion Blood Sampling Arm for obtaining donor samples prior to collection of the Whole Blood Unit.

11.3. Blood bag codes ending in A6 also include a DonorCareTM Needle Guard pre-attached to the donor tubing. DonorCare Needle Guard device instructions are provided on the reverse side.

11.4. The blood bag collection set is made of PVC (polyvinyl chloride with DEHP plasticizer).

11.5. The blood bag has no components made of natural rubber latex.

11.6. Tubing internal diameter (ID) nominal 3.0 mm.

11.7. Tubing outer diameter (OD) nominal 4.4 mm.

11.8. Tubing line maximum 16 segments available.

16. HOW SUPPLIED/STORAGE AND HANDLING

16.1. Single use only.

16.2. Sterile and non-pyrogenic fluid path. Sterilized by steam. Opacity of the blood bag system may be observed. This is due to moisture absorption during the sterilization process. This is normal and does not affect the solution quality or safety. The opacity will diminish gradually.

16.3. A Material Safety Data Sheet (MSDS) is not required for this product.

STORAGE AND HANDLING

16.4. Recommended storage conditions: Room Temperature (15-25°C/59-77°F).

16.5. Avoid excessive heat and direct sunlight. Protect from freezing.

16.6. To open blister package, peel cover film back 4/5 of its length.

16.7. After opening, the blood bag system may be stored at room temperature for 7 days, or it may be stored for 30 days in the blister package after returning the cover film to the original position and sealing with tape to prevent possible loss of moisture.

16.8. Blood bags in the unopened blister package may be used through the last day of the month and year as indicated on the original manufacturer's packaging.

16.9. The AGELESS packet contained in this package absorbs oxygen and generates heat on removal. Do not open and handle it with care.

16.10. Dispose of the AGELESS packet with the blister tray.

16.11. Do not dispose the AGELESS packet with wastes containing volatile or flammable materials.

16.12. For the Quadruple blood bag set, Code BB*LGQ506A6 is supplied 15/case.

MANUFACTURED BY:
TERUMO CORPORATION
44-1, 2-CHOME, HATAGAYA, SHIBUYA-KU,
TOKYO 151-0072, JAPAN MADE IN JAPAN

© TERUMO CORPORATION Nov. 2021

All brand names are trademarks or registered trademarks of TERUMO CORPORATION and their respective owners.

PROCEDURE FOR USE OF DonorCare™ Needle Guard

This device is for use by trained individuals.

Intended Use

The DonorCare Needle Guard is incorporated onto the donor tubing to shield the needle immediately after withdrawal from the donor.

Single Use Only.

Preparation

1. Move the DonorCare on the tubing ensuring that it slides easily and the arrow is pointing toward the needle hub.

2. Ensure that the three lock points on the DonorCare are locked closed.

Whole Blood Collection

3. Perform the phlebotomy as per your institution's standard operating procedures.

4. Slide the DonorCare over the needle hub so that it covers approximately one half to two thirds of the needle hub.

5. Stabilize the DonorCare to the arm by placing a piece of tape over the front end so that the tape does not extend over the front of the DonorCare.

Withdrawal of Needle

Important | The DonorCare must be held stationary while the needle is withdrawn into it.
Caution | The needle must be fully shielded by DonorCare to prevent accidental injury.

6. Hold gauze over the venipuncture site with finger tips without exerting pressure. Hold the sides of the DonorCare near the front with the index finger and thumb of the same hand.

7. With the other hand, hold the donor tubing close behind the DonorCare.

Note: A hemostat may be placed on the tubing behind the DonorCare when the blood collection is complete. This will help to prevent blood drops from forming.

8. Pull tubing smoothly and swiftly with one motion until the needle is locked in place inside the DonorCare.

9. Confirm that the needle is locked by:

1. Listening for two 'clicks' as the needle is drawn into DonorCare.
2. If the clicks are not heard as the needle is drawn into the DonorCare, continue to pull firmly on the tubing to assure needle is fully withdrawn into DonorCare.

10. Visually check that the needle is fully shielded by DonorCare before removing from the donor's arm.

11. Remove the tape from the DonorCare and arm.

12. Apply pressure to the gauze covering the venipuncture site.

Warning | Do not place fingers at the opening of DonorCare after removal from the donor's arm.

Difficult Phlebotomy (Examples may include: Slow blood flow, deep or fine vein, steep angle)

It may be necessary to delay placing the DonorCare over the needle hub until the end of the blood collection. In such situations:

Leave the DonorCare on the tubing behind the needle hub. At the end of the blood collection carefully remove the tape from the needle hub and slide the DonorCare over the hub so that it covers approximately one half to two thirds of the needle hub.

Withdraw the needle into the DonorCare as stated in steps 6. through 12. above.

Rx ONLY

DonorCare is manufactured by ITL Corporation, Melbourne, Australia.

TERUMO CORPORATION
44-1, 2-CHOME, HATAGAYA, SHIBUYA-KU,
TOKYO 151-0072, JAPAN

© TERUMO CORPORATION Nov. 2021

PRINCIPAL DISPLAY PANEL - Kit Case

IMUFLEX™ WB-SP
BLOOD BAG SYSTEM WITH INTEGRAL WHOLE BLOOD LEUKOCYTE
REDUCTION FILTER (SAVING PLATELETS) WITH DIVERSION
BLOOD SAMPLING ARM™

TERUMO

CPD WITH OPTISOL RED CELL PRESERVATIVE SOLUTION
FOR COLLECTION OF 500mL OF BLOOD

Each unit consists of a collection bag containing 70mL of Anticoagulant
CPD solution, with a satellite bag containing 111mL of OPTISOL Red Cell
Preservative Solution.

Each 70mL Anticoagulant CPD solution USP contains 1.79g Dextrose
(monohydrate) USP, 1.84g Sodium Citrate (dihydrate) USP, 209mg Citric
Acid (anhydrous) USP, 156mg Monobasic Sodium Phosphate
(monohydrate) USP.

Each 111mL OPTISOL Red Cell Preservative Solution contains 974mg
Sodium Chloride USP, 1.00g Dextrose (monohydrate) USP, 583mg Mannitol
USP, 33.3mg Adenine USP.

STERILE, NON-PYROGENIC
FLUID PATH.
DO NOT USE UNLESS
SOLUTIONS ARE CLEAR.

NDC:53877-105-06

CODE
LOT No.
EXPIRY
DONOR NEEDLE 16G×½"(1.60×38mm)
UNIT(S)

Rx ONLY

RECOMMENDED STORAGE : Room Temperature (15-25 °C/ 59-77 °F).
Avoid excessive heat. Protect from freezing.
After opening, the blood bag system may be stored at room temperature for 7 days, or
it may be stored for 30 days in the blister package after returning the cover film to the
original position and sealing with tape to prevent loss of moisture.
See Instructions For Use.

Manufactured by : TERUMO CORPORATION Tokyo, Japan
All brand names are trademarks or registered trademarks owned by TERUMO CORPORATION,
its affiliates, or unrelated third parties.

Rev. 2024-07
SC-4-HS6-A6 ②